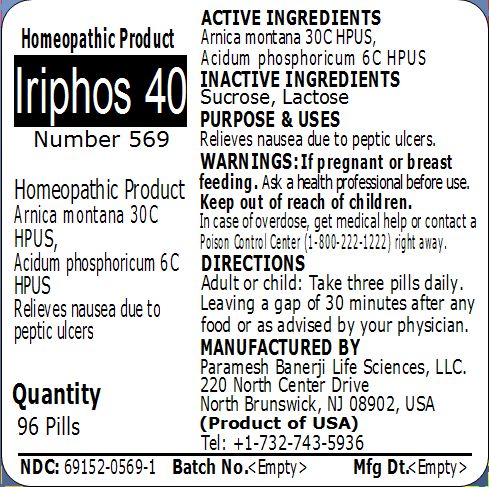 DRUG LABEL: Iriphos 40 Number 569
NDC: 69152-0569 | Form: PELLET
Manufacturer: Paramesh Banerji Life Sciences LLC
Category: homeopathic | Type: HUMAN OTC DRUG LABEL
Date: 20150303

ACTIVE INGREDIENTS: ARNICA MONTANA 30 [hp_C]/1 1; PHOSPHORIC ACID 6 [hp_C]/1 1
INACTIVE INGREDIENTS: SUCROSE; LACTOSE

Active Ingredients

Arnica montana 30C HPUS, Acidum phosphoricum 6C HPUS

Inactive Ingredients

Sucrose, Lactose

Purpose

Relieves nausea due to peptic ulcers

Uses

Relieves nausea due to peptic ulcers

Warnings

If pregnant or breast feeding ask a health professional before use.

Keep out of reach of children. In case of overdose, get medical help or contact a Poison Control Center (1-800-222-1222) right away.

Direction

Adult or child: Take three pills daily. Leaving a gap of 30 minutes after any food or as advised by your physician.

Manufactured by

Paramesh Banerji Life Sciences, LLC

220 North Center Drive

North Brunswick, NJ 08902, USA

Product of USA

Tel: +1-732-743-5936

Principal Display Panel

Homeopathic Product

Iriphos 40

Number 569

Homeopathic Product

Arnica montana 30C HPUS, Acidum phosphoricum 6C HPUS

Relieves nausea due to peptic ulcers

Quantity

96 Pills